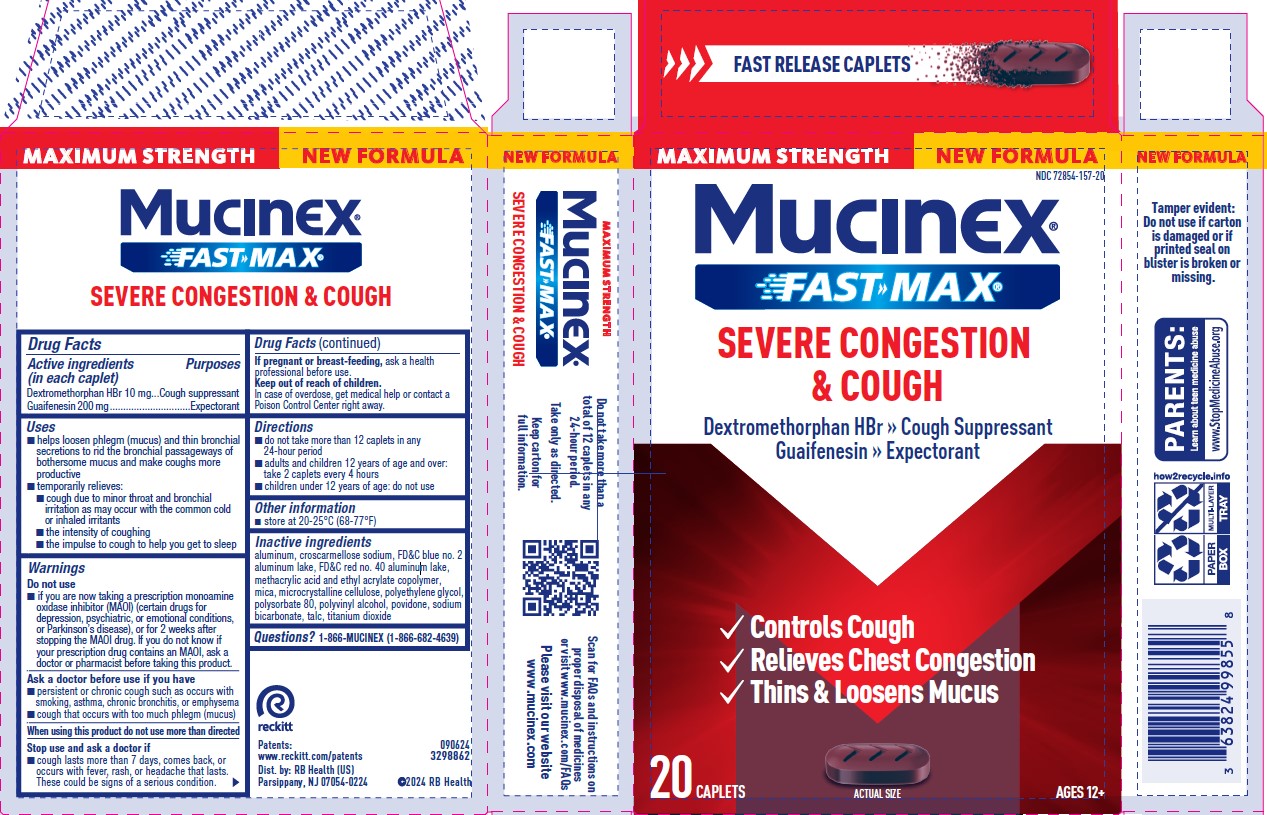 DRUG LABEL: Mucinex Fast-Max
NDC: 72854-157 | Form: TABLET, COATED
Manufacturer: RB Health (US) LLC
Category: otc | Type: HUMAN OTC DRUG LABEL
Date: 20250410

ACTIVE INGREDIENTS: GUAIFENESIN 200 mg/1 1; DEXTROMETHORPHAN HYDROBROMIDE 10 mg/1 1
INACTIVE INGREDIENTS: METHACRYLIC ACID AND ETHYL ACRYLATE COPOLYMER; CROSCARMELLOSE SODIUM; FD&C BLUE NO. 2; ALUMINUM; FD&C RED NO. 40; MICA; MICROCRYSTALLINE CELLULOSE; POLYETHYLENE GLYCOL 3350; POLYSORBATE 80; POLYVINYL ALCOHOL, UNSPECIFIED; POVIDONE K30; SODIUM BICARBONATE; TALC; TITANIUM DIOXIDE

Mucinex® Fast-Max®Severe Congestion and Cough

Drug Facts

ACTIVE INGREDIENT

Dextromethorphan HBr 10 mg
Guaifenesin 200 mg

PURPOSE

Active ingredients (in each caplet) | Purposes
Dextromethorphan HBr 10 mg | Cough suppressant
Guaifenesin 200 mg | Expectorant

Uses

- helps loosen phlegm (mucus) and thin bronchial secretions to rid the bronchial passageways of bothersome mucus and make coughs more productive
- temporarily relieves:
  - cough due to minor throat and bronchial irritation as may occur with the common cold or inhaled irritants
  - the intensity of coughing
  - the impulse to cough to help you get to sleep
  - nasal congestion due to a cold

Warnings

Do not use

- if you are now taking a prescription monoamine oxidase inhibitor (MAOI) (certain drugs for depression, psychiatric, or emotional conditions, or Parkinson's disease), or for 2 weeks after stopping the MAOI drug. If you do not know if your prescription drug contains an MAOI, ask a doctor or pharmacist before taking this product.

Ask a doctor before use if you have

- heart disease
- diabetes
- high blood pressure
- thyroid disease
- trouble urinating due to an enlarged prostate gland
- persistent or chronic cough such as occurs with smoking, asthma, chronic bronchitis, or emphysema
- cough that occurs with too much phlegm (mucus)

When using this product do not use more than directed

Stop use and ask a doctor if

- nervousness, dizziness, or sleeplessness occur
- symptoms do not get better within 7 days or occur with fever
- cough comes back, or occurs with fever, rash, or headache that lasts. These could be signs of a serious condition.

PREGNANCY OR BREAST FEEDING

If pregnant or breast-feeding,ask a health professional before use.

Keep out of reach of children.

In case of overdose, get medical help or contact a Poison Control Center right away.

Directions

- do not take more than 12 caplets in any 24-hour period
- adults and children 12 years of age and over: take 2 caplets every 4 hours
- children under 12 years of age: do not use

Other information

- store at 20-25°C (68-77°F)

Inactive ingredients

aluminum, croscarmellose sodium, FD&C blue no. 2

aluminum lake, FD&C red no. 40 aluminum lake,
methacrylic acid and ethyl acrylate copolymer,
mica, microcrystalline cellulose, polyethylene glycol,
polysorbate 80, polyvinyl alcohol, povidone, sodium
bicarbonate, talc, titanium dioxide

Questions?

1-866-MUCINEX (1-866-682-4639)You may also report side effects to this phone number.

Dist. by: RB Health (US)
Parsippany, NJ 07054-0224

Principal Display Panel - 20 Caplet Blister Pack Carton

NDC 63824-157-20